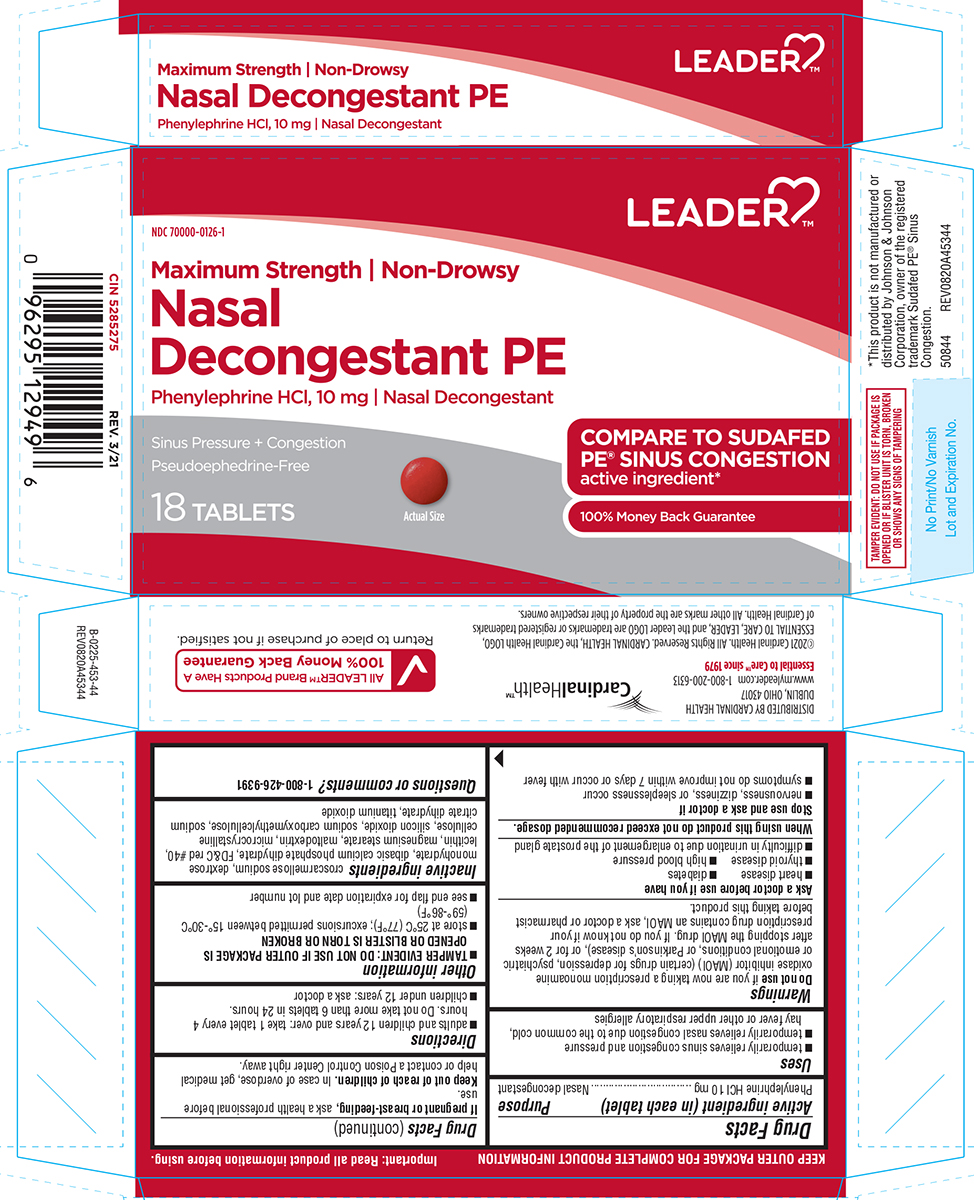 DRUG LABEL: Nasal Decongestant PE
NDC: 70000-0126 | Form: TABLET, FILM COATED
Manufacturer: Cardinal Health 110, LLC. DBA Leader
Category: otc | Type: HUMAN OTC DRUG LABEL
Date: 20251006

ACTIVE INGREDIENTS: PHENYLEPHRINE HYDROCHLORIDE 10 mg/1 1
INACTIVE INGREDIENTS: CROSCARMELLOSE SODIUM; DEXTROSE MONOHYDRATE; DIBASIC CALCIUM PHOSPHATE DIHYDRATE; FD&C RED NO. 40; LECITHIN, SOYBEAN; MAGNESIUM STEARATE; MALTODEXTRIN; MICROCRYSTALLINE CELLULOSE; SILICON DIOXIDE; CARBOXYMETHYLCELLULOSE SODIUM, UNSPECIFIED; TRISODIUM CITRATE DIHYDRATE; TITANIUM DIOXIDE

Leader 44-453

Active ingredient (in each tablet)

Phenylephrine HCl 10 mg

Purpose

Nasal decongestant

Uses

- temporarily relieves nasal congestion due to the common cold, hay fever or other upper respiratory allergies
- temporarily relieves sinus congestion and pressure

Warnings

Do not use

if you are now taking a prescription monoamine oxidase inhibitor (MAOI) (certain drugs for depression, psychiatric or emotional conditions, or Parkinson's disease), or for 2 weeks after stopping the MAOI drug. If you do not know if your prescription drug contains an MAOI, ask a doctor or pharmacist before taking this product.

Ask a doctor before use if you have

- diabetes
- heart disease
- high blood pressure
- thyroid disease
- difficulty in urination due to enlargement of the prostate gland

When using this product

do not exceed recommended dosage.

Stop use and ask a doctor if

- nervousness, dizziness, or sleeplessness occur
- symptoms do not improve within 7 days or occur with fever

If pregnant or breast-feeding,

ask a health professional before use.

Keep out of reach of children.

In case of overdose, get medical help or contact a Poison Control Center right away.

Directions

- adults and children 12 years and over: take 1 tablet every 4 hours. Do not take more than 6 tablets in 24 hours.
- children under 12 years: ask a doctor

Other information

- TAMPER EVIDENT: DO NOT USE IF OUTER PACKAGE IS OPENED OR BLISTER IS TORN OR BROKEN
- store at 25ºC (77ºF); excursions permitted between 15º-30ºC (59º-86ºF)
- see end flap for expiration date and lot number

Inactive ingredients

croscarmellose sodium, dextrose monohydrate, dibasic calcium phosphate dihydrate, FD&C red #40, lecithin, magnesium stearate, maltodextrin, microcrystalline cellulose, silicon dioxide, sodium carboxymethylcellulose, sodium citrate dihydrate, titanium dioxide

Questions or comments?

1-800-426-9391

Principal display panel

LEADER™

NDC 70000-0126-1

Maximum Strength | Non-Drowsy

Nasal
Decongestant PE
Phenylephrine HCl, 10 mg | Nasal Decongestant

Sinus Pressure + Congestion
Pseudoephedrine-Free

18 TABLETS

Actual size

COMPARE TO SUDAFED
PE® SINUS CONGESTION
active ingredient*

100% Money Back Guarantee

TAMPER EVIDENT: DO NOT USE IF PACKAGE IS
OPENED OR IF BLISTER UNIT IS TORN, BROKEN
OR SHOWS ANY SIGNS OF TAMPERING

*This product is not manufactured or
distributed by Johnson & Johnson
Corporation, owner of the registered
trademark Sudafed PE® Sinus
Congestion.
50844 REV0820A45323

CardinalHealth™

DISTRIBUTED BY CARDINAL HEALTH
DUBLIN, OHIO 43017
www.myleader.com 1-800-200-6313
Essential to Care™ since 1979

©2021 Cardinal Health. All Rights Reserved. CARDINAL HEALTH, the Cardinal Health LOGO, ESSENTIAL TO CARE, LEADER, and the Leader LOGO are trademarks or registered trademarks of Cardinal Health. All other marks are the property of their respective owners.

All LEADER™ Brand Products Have A
100% Money Back Guarantee
Return to place of purchase if not satisfied.

44-453